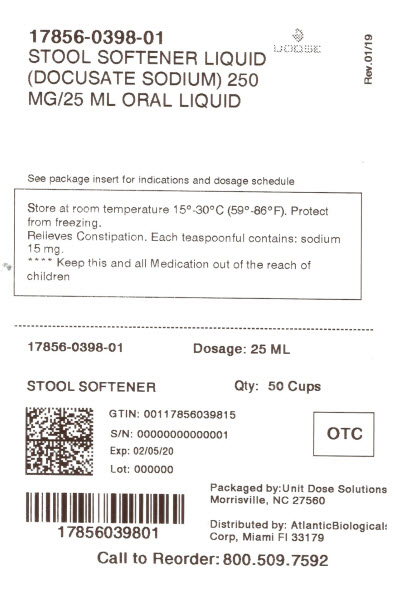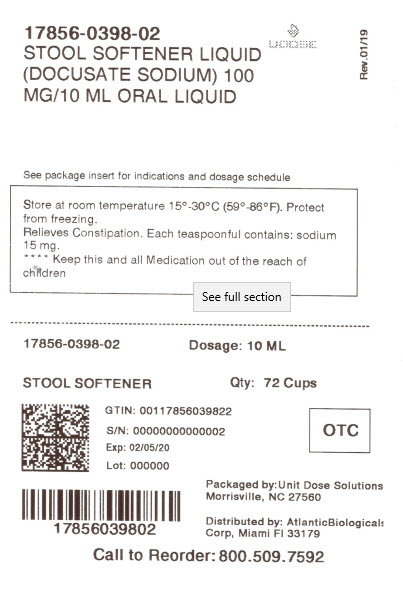 DRUG LABEL: Stool Softener Liquid
NDC: 17856-0398 | Form: LIQUID
Manufacturer: ATLANTIC BIOLOGICALS CORP.
Category: otc | Type: HUMAN OTC DRUG LABEL
Date: 20210118

ACTIVE INGREDIENTS: DOCUSATE SODIUM 50 mg/5 mL
INACTIVE INGREDIENTS: ANHYDROUS CITRIC ACID; D&C RED NO. 33; METHYLPARABEN; PROPYLPARABEN; POLYETHYLENE GLYCOL; SODIUM CITRATE; WATER; POLOXAMER 407; SUCROSE; SORBITOL

GNP DOCUSATE LIQUID

Active ingredient (in each 5 mL teaspoonful)

Docusate Sodium 50 mg

Purpose

Stool Softener Laxative

Uses

- relieves occasional constipation (irregularity)
- generally produces bowel movement in 12 to 72 hours

Warnings

Do not use for more than one week unless directed by a doctor

Ask a doctor before use if you

- have abdominal pain, nausea, or vomiting
- are taking mineral oil
- have noticed a sudden change in bowel habits that lasts more than 14 days

Stop use and ask a doctor if

- you have rectal bleeding or failure to have a bowel movement within 3 days. These could be signs of a serious condition.
- a skin rash occurs
- you experience throat irritation

PREGNANCY OR BREAST FEEDING

If pregnant or breast feeding, ask a health professional before use.

Keep out of reach of children. In case of overdose, get medical help or contact a poison control Center right away.

Directions

- follow dosing directions below or take as directed by doctor
- must be given in a 6 to 8 oz glass of milk or fruit juice to prevent throat irritation
- may be taken as a single daily dose or in divided doses
- take maximum daily dose until first bowel movement, then reduce dose according to individual response
- shake well before using

Adults and children 12 years and over | 1 to 4 teaspoonfuls (5 to 20 mL)
Children under 12 years of age | ask a doctor

Other information

- Each teaspoonful contains: sodium 15 mg
- Store at room temperature 15°- 30° C (59°-86° F)
- protect from excessive heat
- Keep tightly closed

Inactive ingredients

citric acid, D&C Red #33, flavor, parabens, poloxamer, polyethylene glycol, sodium citrate, sorbitol, sucrose, and water.

DISTRIBUTED BY:

ATLANTIC BIOLOGICALS CORP.

20101 N.E 16TH PLACE

MIAMI, FL 33179

package label

NDC 17856-0398-1

Compare to Colace® Liquid active ingredient *

GOOD NEIGHBOR PHARMACY

STOOL
SOFTENER
LIQUID
Docusate Sodium
Relieves Constipation
250mg/25 mL

50 cups per case

NDC 17856-0398-2

Compare to Colace® Liquid active ingredient *

GOOD NEIGHBOR PHARMACY

STOOL
SOFTENER
LIQUID
Docusate Sodium
Relieves Constipation
100mg/10 mL

72 cups per case